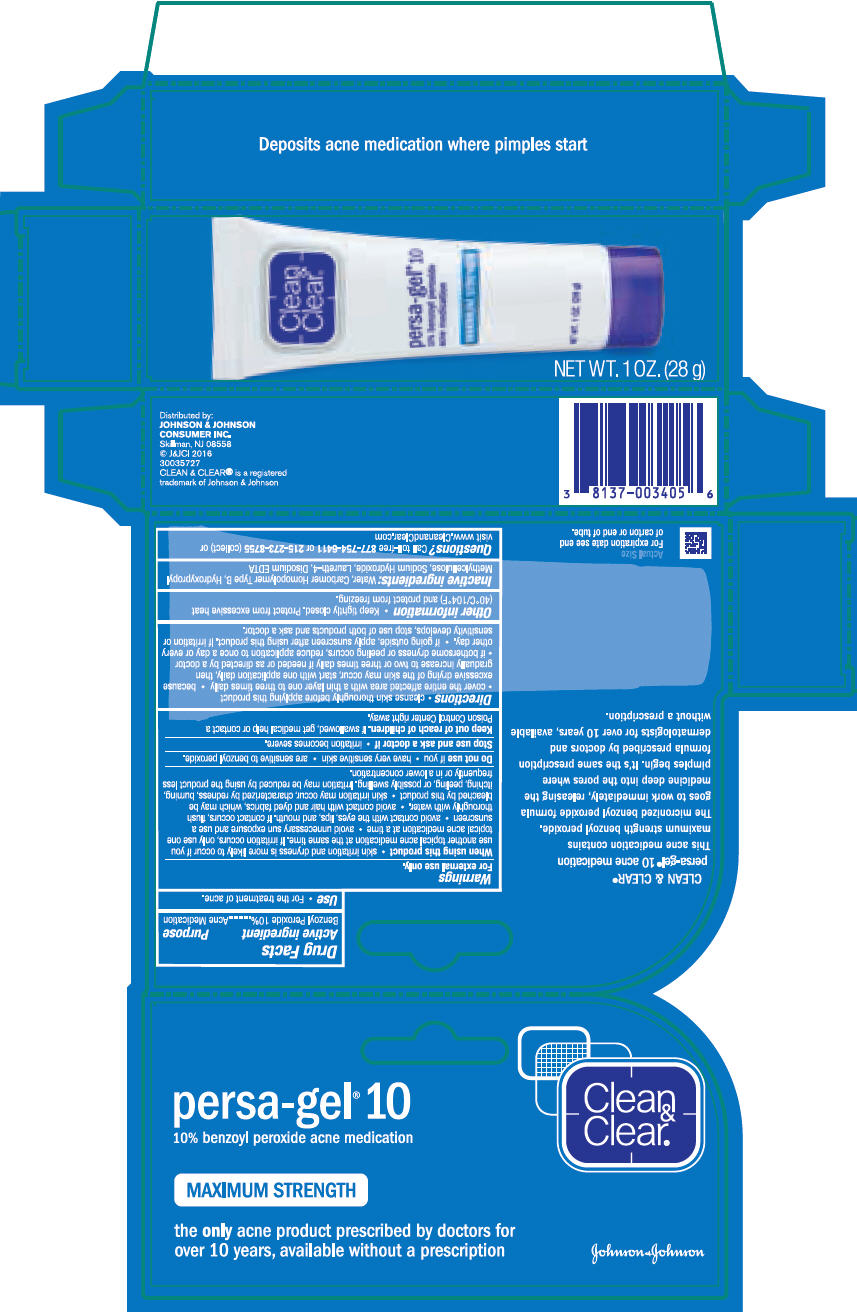 DRUG LABEL: Clean and Clear Persa-Gel 10
NDC: 69968-0212 | Form: GEL
Manufacturer: Kenvue Brands LLC
Category: otc | Type: HUMAN OTC DRUG LABEL
Date: 20241106

ACTIVE INGREDIENTS: BENZOYL PEROXIDE 100 mg/1 g
INACTIVE INGREDIENTS: WATER; CARBOMER HOMOPOLYMER TYPE B (ALLYL PENTAERYTHRITOL OR ALLYL SUCROSE CROSSLINKED); HYPROMELLOSE, UNSPECIFIED; SODIUM HYDROXIDE; LAURETH-4; EDETATE DISODIUM ANHYDROUS

Clean & Clear® persa-gel® 10

Drug Facts

Active ingredient

Benzoyl Peroxide 10%

Purpose

Acne medication

Use

For the treatment of acne.

Warnings

For external use only.

When using this product

- skin irritation and dryness is more likely to occur if you use another topical acne medication at the same time. If irritation occurs, only use one topical acne medication at a time.
- avoid unnecessary sun exposure and use a sunscreen
- avoid contact with the eyes, lips, and mouth. If contact occurs, flush thoroughly with water.
- avoid contact with hair and dyed fabrics, which may be bleached by this product
- skin irritation may occur, characterized by redness, burning, itching, peeling, or possibly swelling. Irritation may be reduced by using the product less frequently or in a lower concentration .

Do not use if you

- have very sensitive skin
- are sensitive to benzoyl peroxide.

Stop use and ask a doctor if

- irritation becomes severe .

Keep out of reach of children. If swallowed, get medical help or contact a Poison Control Center right away.

Directions

- cleanse skin thoroughly before applying this product
- cover the entire affected area with a thin layer one to three times daily
- because excessive drying of the skin may occur, start with one application daily, then gradually increase to two or three times daily if needed or as directed by a doctor
- if bothersome dryness or peeling occurs, reduce application to once a day or every other day.
- if going outside, apply sunscreen after using this product. If irritation or sensitivity develops, stop use of both products and ask a doctor.

Other information

Keep tightly closed. Protect from excessive heat (40°C/104°F) and protect from freezing.

Inactive ingredients

Water, Carbomer Homopolymer Type B, Hydroxypropyl Methylcellulose, Sodium Hydroxide, Laureth-4, Disodium EDTA

Questions?

Call toll-free 877-754-6411 or 215-273-8755 (collect) or visit www.CleanandClear.com

Distributed by:
JOHNSON & JOHNSON
CONSUMER INC.
Skillman, NJ 08558

PRINCIPAL DISPLAY PANEL

Clean
&
Clear®

persa-gel® 10
10% benzoyl peroxide acne medication

MAXIMUM STRENGTH

The only acne product prescribed by doctors for
over 10 years, available without a prescription
Johnson & Johnson
NET WT. 1 OZ. (28 g)